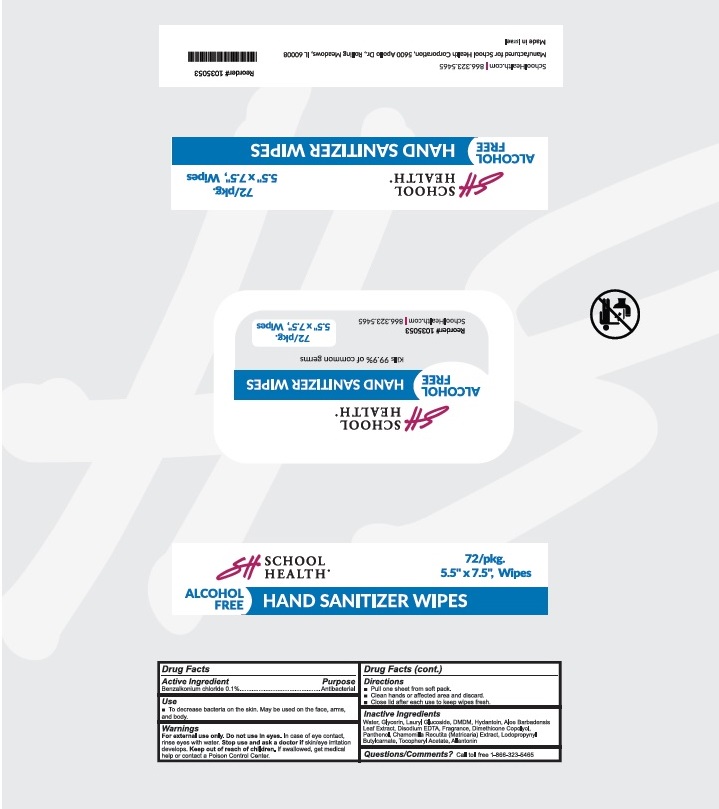 DRUG LABEL: School Health Alcohol-free Hand Sanitizer Wipes
NDC: 76123-200 | Form: CLOTH
Manufacturer: School Health Corporation
Category: otc | Type: HUMAN OTC DRUG LABEL
Date: 20230612

ACTIVE INGREDIENTS: BENZALKONIUM CHLORIDE 0.1 g/1 1
INACTIVE INGREDIENTS: WATER; GLYCERIN; LAURYL GLUCOSIDE; DMDM HYDANTOIN; ALOE VERA LEAF; EDETATE DISODIUM ANHYDROUS; PEG/PPG-18/18 DIMETHICONE; PANTHENOL; MATRICARIA CHAMOMILLA WHOLE; IODOPROPYNYL BUTYLCARBAMATE; .ALPHA.-TOCOPHEROL ACETATE; ALLANTOIN

School Health Alcohol Free Hand Sanitizer Wipes

DRUG FACTS

Active Ingredient

Benzalkonium Chloride 0.1%

Purpose

Antibacterial

USE

■ To decrease bacteria on the. May be used on the face, arms, and body.

Warning

For external use only.
Do not use in eyes. In case of eyes contact,
rinse with water.
Stop use and ask a doctor if skin/eye irritation
develops.

Keep out of reach of children.
If swallowed, get medical help or contact a Poison Control Center.

Directions

■ Pull one sheet from soft pack.

■ Clean hands of affected area and discard.

■ Close lid after each use to keep wipes fresh.

Inactive ingredients

Water, Glycerin, Lauryl Glucoside, DMD, Hydantoin, Aloe barbadensis

Leaf Extract, Disodium EDTA, Fragrance, Dimethicone Copolyol,

Panthenol, Chamomilla Recutita (Matricaria) Extract, Lodopropynl

Butylcarnate, Tocopheryl Acetate, Allantonin

QUESTIONS

Questions/Comments? Call toll free 1-866-323-5465

School Health Alcohol Free Hand Sanitizer Wipes Labeling

School Health

Alcohol Free Hand Sanitizer Wipes

72/pkg.

5.5" x 7.5", Wipes

Manufactured for School Health Corporation, 5600 Apollo Dr., Rolling Meadows, IL 60008

reg